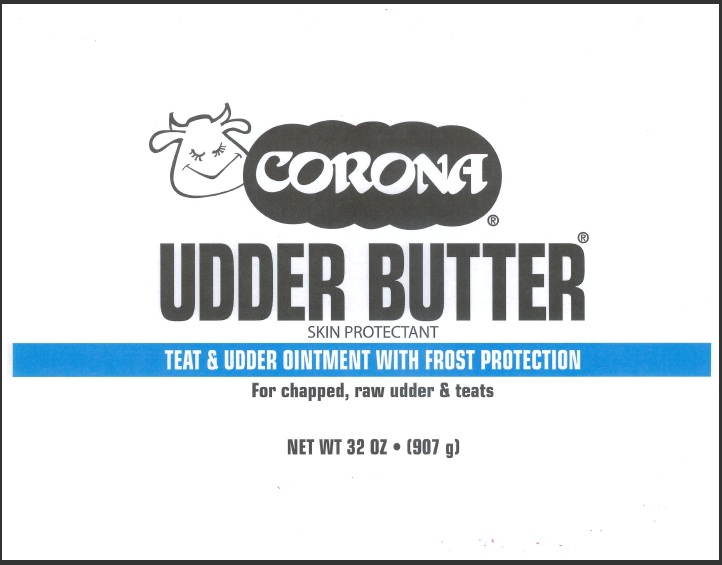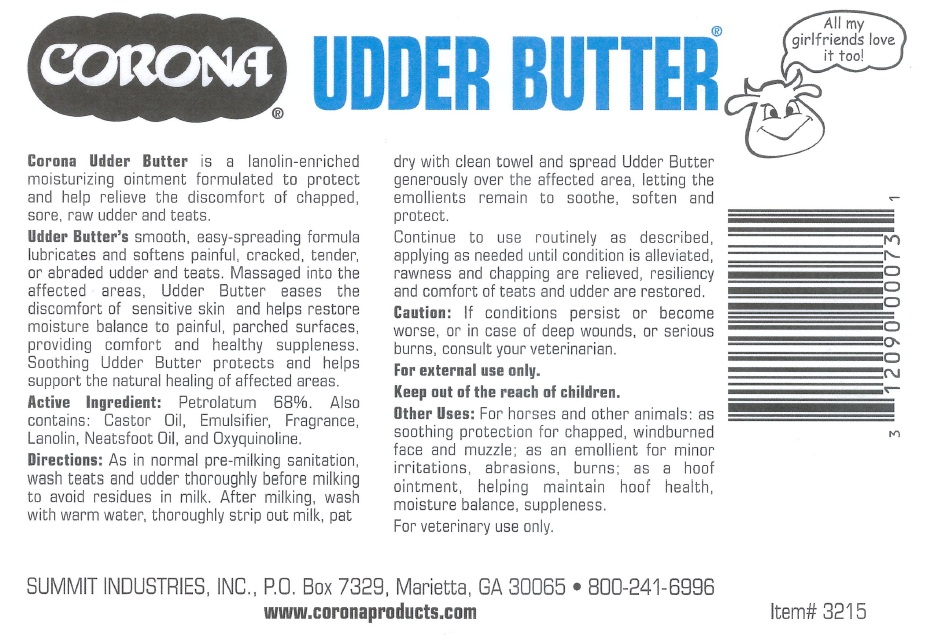 DRUG LABEL: CORONA UDDER BUTTER
NDC: 12090-0031 | Form: OINTMENT
Manufacturer: SUMMIT INDUSTRIES, INC.
Category: animal | Type: OTC ANIMAL DRUG LABEL
Date: 20101108

ACTIVE INGREDIENTS: PETROLATUM 68 g/100 g
INACTIVE INGREDIENTS: CASTOR OIL; LANOLIN; OXYQUINOLINE

CORONA UDDER BUTTER

Active Ingredient: Petrolatum 68%

PURPOSE

Corona Udder Butter is a lanolin-enriched moisturizing ointment formulated to protect and help relieve the discomfort of chapped, sore, raw udder and teats.

INDICATIONS AND USAGE

to protect and relieve the discomfort of chapped sore, raw udder and teats.

DOSAGE AND ADMINISTRATION

As in normal pre-milking sanitation, wash teats and udder thoroughly before milking to avoid residues in milk. After milking, wash with warm water, throughly strip out milk, pat dry with clean towel and spread Udder Butter generously over the affected area, letting the emollients remain to soothe, soften and protect.

Continue to use routinely as described, applying as needed until condition is alleviated, rawness and chapping are relieved, resiliency and comfort of teats and udder are restored.

DESCRIPTION

Udder Butter's smooth, easy-spreading formula lubricates and softens painful, cracked, tender, or abraded udder and teats. Massaged into the affected areas, Udder Butter eases the discomfort of sensitive skin and helps restore moisture balance to painful, parched surfaces, providing comfort and healthy suppleness. soothing Udder Butter protects and helps support the natural healing of affective areas.

INACTIVE INGREDIENT

Also contains: Castor Oil, Emulsifier, Fragrance, lanolin, Neatsfoot Oil, and Oxyquinoline

WARNINGS

Caution: If conditions persist or become worse, or in case of deep wounds, or serious burns, consult your veterinarian

For external use only.

Keep out of the reach of children.

INDICATIONS AND USAGE

For horses and other animals: as soothing protection for chapped, windburned face and muzzle; as an emollient for minor irritations, abrasions, and burns; as a hoof hointment, helping maintain hoof health, moisture balance, supplenss.

For veterinary use only.

DESCRIPTION

SUMMIT INDUSTRIES, INC., PO BOX 7329 MARIETTA, GA 30065

800-241-6996

www.coronaproducts.com